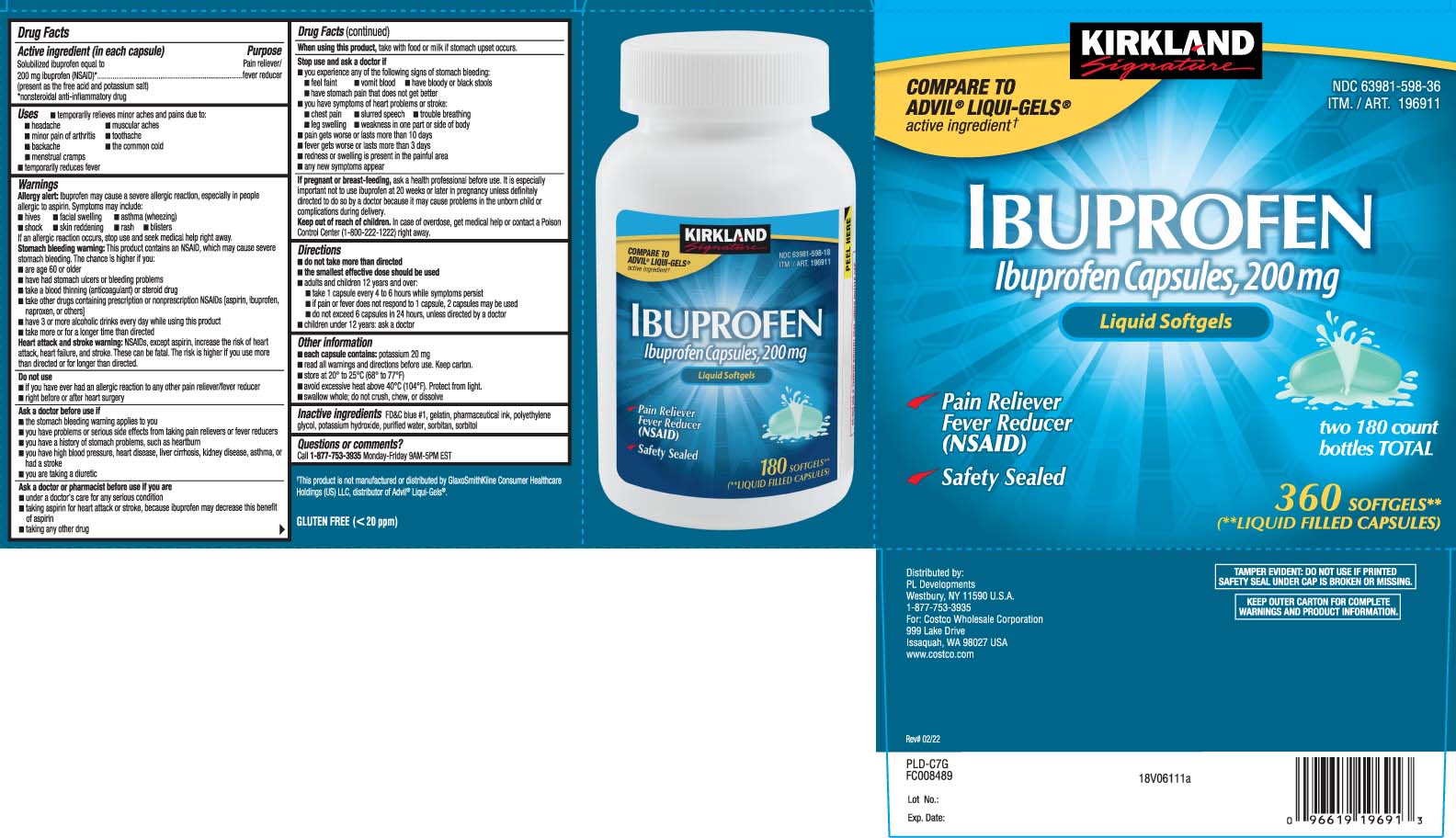 DRUG LABEL: Ibuprofen
NDC: 63981-598 | Form: CAPSULE, LIQUID FILLED
Manufacturer: Costco Wholesale
Category: otc | Type: HUMAN OTC DRUG LABEL
Date: 20260120

ACTIVE INGREDIENTS: IBUPROFEN 200 mg/1 1
INACTIVE INGREDIENTS: FD&C BLUE NO. 1; GELATIN; POLYETHYLENE GLYCOL, UNSPECIFIED; POTASSIUM HYDROXIDE; WATER; SORBITAN; SORBITOL

Drug Facts

Active ingredient (in each capsule)

Solubilized ibuprofen equal to 200 mg ibuprofen (NSAID)*
(present as the free acid and potassium salt)

*nonsteroidal anti-inflammatory drug

Purpose

Pain reliever/fever reducer

Uses

- temporarily relieves minor aches and pains due to:
  - headache
  - muscular aches
  - minor pain of arthritis
  - toothache
  - backache
  - the common cold
  - menstrual cramps
- temporarily reduces fever

Warnings

Allergy alert: Ibuprofen may cause a severe allergic reaction, especially in people allergic to aspirin. Symptoms may include:

- hives
- facial swelling
- asthma (wheezing)
- shock
- skin reddening
- rash
- blisters

If an allergic reaction occurs, stop use and seek medical help right away.

Stomach bleeding warning: This product contains an NSAID, which may cause severe stomach bleeding. The chance is higher if you:

- are age 60 or older
- have had stomach ulcers or bleeding problems
- take a blood thinning (anticoagulant) or steroid drug
- take other drugs containing prescription or nonprescription NSAIDs (aspirin, ibuprofen, naproxen, or others)
- have 3 or more alcoholic drinks every day while using this product
- take more or for a longer time than directed

Heart attack and stroke warning: NSAIDs, except aspirin, increase the risk of heart attack, heart failure, and stroke. These can be fatal. The risk is higher if you use more than directed or for longer than directed

Do not use

- if you have ever had an allergic reaction to any other pain reliever/fever reducer
- right before or after heart surgery

Ask a doctor before use if

- the stomach bleeding warning applies to you
- you have problems or serious side effects from taking pain relievers or fever reducers
- you have a history of stomach problems, such as heartburn
- you have high blood pressure, heart disease, liver cirrhosis, kidney disease, asthma or had a stroke
- you are taking a diuretic

Ask a doctor or pharmacist before use if you are

- under a doctor's care for any serious condition
- taking aspirin for heart attack or stroke, because ibuprofen may decrease this benefit of aspirin
- taking any other drug

When using this product

- take with food or milk if stomach upset occurs

Stop use and ask a doctor if

- you experience any of the following signs of stomach bleeding:
  - feel faint
  - vomit blood
  - have bloody or black stools
  - have stomach pain that does not get better
- you have symptoms of heart problems or stroke:
  - chest pain
  - slurred speech
  - trouble breathing
  - leg swelling
  - weakness in one part or side of body
- pain gets worse or last more than 10 days
- fever gets worse or last more than 3 days
- redness or swelling is present in the painful area
- any new symptoms appear

If pregnant or breast-feeding,

ask a health professional before use. It is especially important not to use ibuprofen at 20 weeks or later in pregnancy unless definitely directed to do so by a doctor because it may cause problems in the unborn child or complications during delivery.

Keep out of reach of children.

In case of overdose, get medical help or contact a Poison Control Center (1-800-222-1222) right away

Directions

- do not take more than directed
- the smallest effective dose should be used
- adults and children 12 years and over:
  - take 1 capsule every 4 to 6 hours while symptoms persist
  - if pain or fever does not respond to 1 capsule, 2 capsules may be used
  - do not exceed 6 capsules in 24 hours, unless directed by a doctor
- children under 12 years: ask a doctor

Other information

- each capsule contains: potassium 20 mg
- read all warnings and directions before use. Keep carton.
- store at 20º to 25ºC (68º to 77ºF)
- avoid excessive heat above 40ºC (104ºF). Protect from light.
- swallow whole; do not crush, chew, or dissolve

Inactive ingredients

FD&C blue #1, gelatin, pharmaceutical ink, polyethylene glycol, potassium hydroxide, purified water, sorbitan, sorbitol

Questions or comments?

Call 1-877-753-3935 Monday-Friday 9AM-5PM EST

Principal display panel

COMPARE TO ADVIL® LIQUI-GELS® active ingredient†

IBUPROFEN

Ibuprofen Capsules, 200 mg

Liquid Softgels

Pain Reliever Fever Reducer (NSAID)

Safety Sealed

SOFTGELS**

(**LIQUID-FILLED CAPSULES)

†this product is not manufactured or distributed by GlaxoSmithKline Consumer Healthcare Holdings (US) LLC, distributor of Advil® Liqui-Gels®.

TAMPER EVIDENT: DO NOT USE IF PRINTED SAFETY SEAL UNDER CAP IS BROKEN OR MISSING.

KEEP OUTER CARTON FOR COMPLETE WARNINGS AND PRODUCT INFORMATION.

Distributed by:

PL Developments

Westbury, NY 11590 U.S.A.

For Costco Wholesale Corporation

999 Lake Drive

Issaquah, WA 98027

www.costco.com

Package Label

KIRKLAND SIGNATURE Ibuprofen 200 mg Capsules